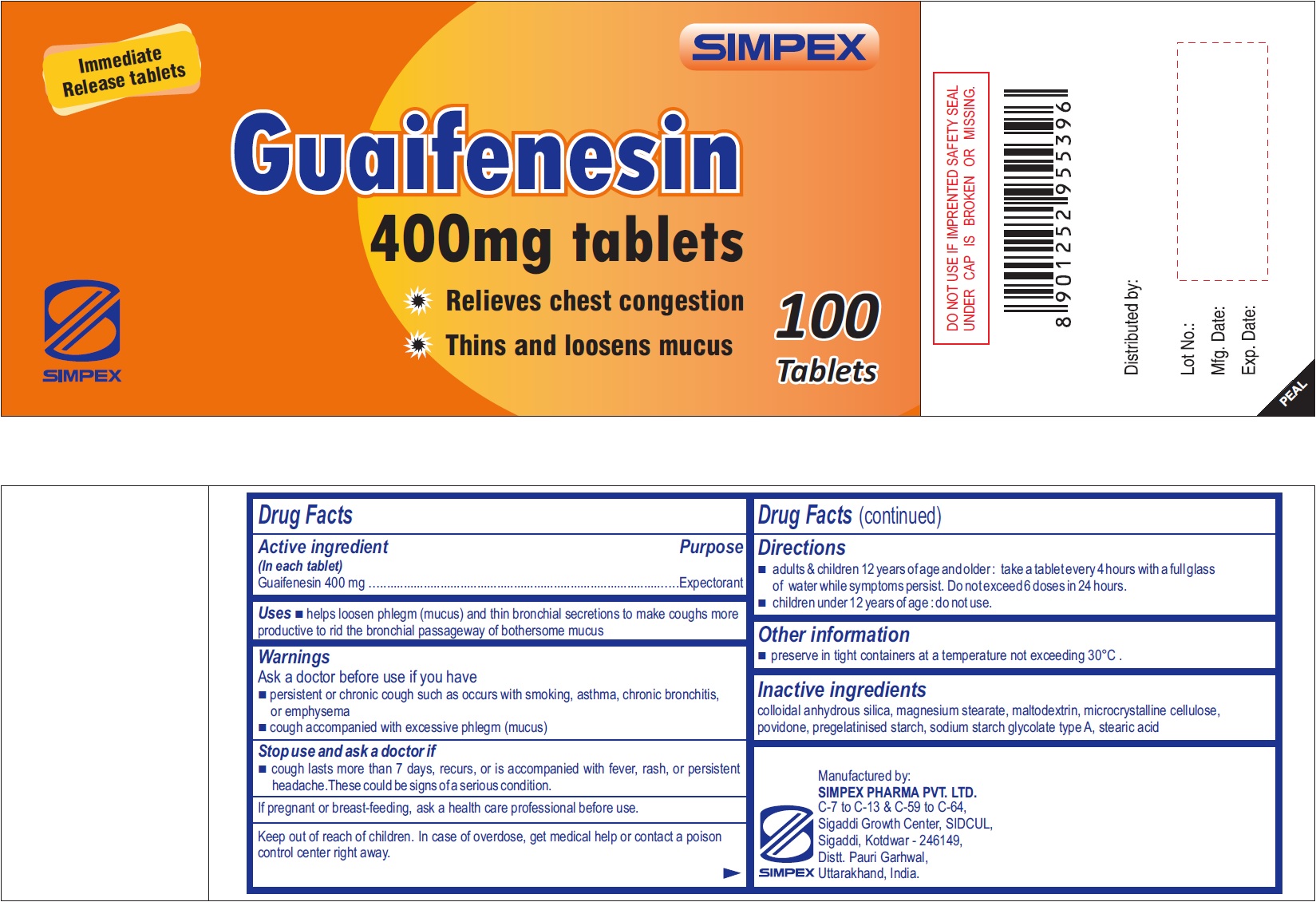 DRUG LABEL: SIMPEX Guaifenesin

NDC: 76457-004 | Form: TABLET
Manufacturer: Simpex Pharma Pvt. Ltd
Category: otc | Type: HUMAN OTC DRUG LABEL
Date: 20231129

ACTIVE INGREDIENTS: GUAIFENESIN 400 mg/1 1
INACTIVE INGREDIENTS: SILICON DIOXIDE; MAGNESIUM STEARATE; MALTODEXTRIN; MICROCRYSTALLINE CELLULOSE; POVIDONE; STEARIC ACID

SIMPEX Guaifenesin

Active ingredient (in each tablet)

Guaifenesin 400 mg

Purpose

Expectorant

Uses

- helps loosen phlegm (mucus) and thin bronchial secretions to make coughs more productive to rid the bronchial passageway of bothersome mucus

Warnings

Ask a doctor before use if you have

- persistent or chronic cough such as occurs with smoking, asthma, chronic bronchitis, or emphysema
- cough accompanied with excessive phlegm (mucus)

Stop use and ask a doctor if

- cough lasts more than 7 days, recurs, or is accompanied with fever, rash, or persistent headache.These could be signs of a serious condition.

If pregnant or breast-feeding,

ask a health care professional before use.

Keep out of reach of children.

In case of overdose, get medical help or contact a poison control center right away.

Directions

- adults & children 12 years of age and older : take a tablet every 4 hours with a full glass of water while symptoms persist. Do not exceed 6 doses in 24 hours.
- children under 12 years of age : do not use.

Other information

- preserve in tight containers at a temperature not exceeding 30°C.

Inactive ingredients

colloidal anhydrous silica, magnesium stearate, maltodextrin, microcrystalline cellulose, povidone, pregelatinised starch, sodium starch glycolate type A, stearic acid